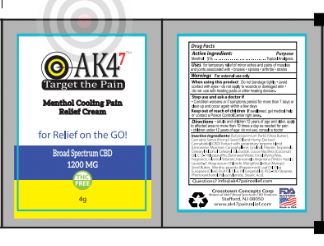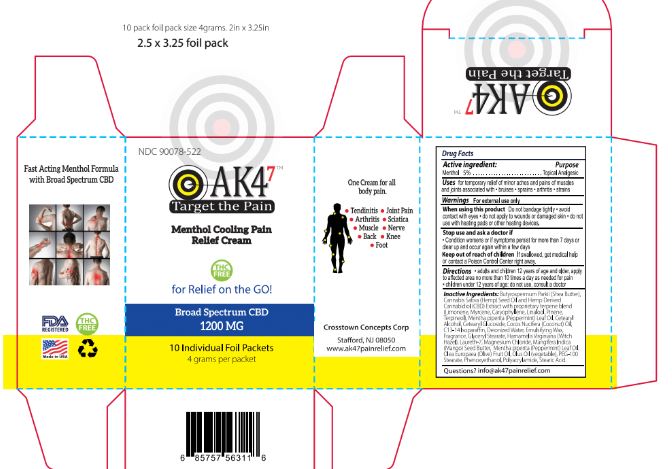 DRUG LABEL: AK47 Menthol Cooling Cream Packet
NDC: 76348-576 | Form: CREAM
Manufacturer: RENU LABORATORIES, INC.
Category: otc | Type: HUMAN OTC DRUG LABEL
Date: 20200825

ACTIVE INGREDIENTS: MENTHOL 0.2 g/4 g
INACTIVE INGREDIENTS: MYRCENE; LINALOOL, (+)-; WHITE WAX; COCONUT OIL; C13-14 ISOPARAFFIN; PEPPERMINT OIL; CETEARYL GLUCOSIDE; OLIVE OIL; PEG-100 STEARATE; PHENOXYETHANOL; POLYACRYLAMIDE (10000 MW); STEARIC ACID; WATER; CANNABIDIOL; GLYCERYL MONOSTEARATE; WITCH HAZEL; SHEA BUTTER; CANNABIS SATIVA SEED OIL; LIMONENE, (+)-; CARYOPHYLLENE; PINENE; TERPINEOL; MAGNESIUM CHLORIDE; CORN OIL; MANGIFERA INDICA SEED BUTTER; CETOSTEARYL ALCOHOL

AK4^7 MENTHOL COOLING CREAM PACKET

Active Ingredient

Menthol 5 %

Purpose

Topical Analgesic

Uses

for temporary relief of minor aches and pains of muscles and joints associated with

- bruises
- sprains
- arthritis
- strains

When using this product

Do not bandage tightly

- avoid contact with eyes
- do not apply to wounds or damaged skin
- do not use with heating pads or other heating devices

Stop use and ask a doctor if

- Condition worsens or if symptoms persist for more than 7 days or clear up and occur again within a few days

Keep out of reach of children

If swallowed, get medical help or contact a Poison Control Center right away.

Directions

- adults and children 12 years of age and older, apply to affected area no more than 10 times a day as needed for pain.
- children under 12 years of age, do not use, consult a doctor.

INACTIVE INGREDIENT

Butyrospermum Parkii (Shea Butter), Cannabis Sativa (Hemp) Seed Oil and Hemp Derived Cannabidiol (CBD) with proprietary terpene blend (Limonene, Myrcene, Caryophyllene, Linalool, Pinene, Terpineol), Cetearyl Alcohol, Cetearyl Glucoside, Cocos Nucifera (Coconut) Oil, C13-14 Isoparaffin, Deionized Water, Emulsifying Wax, Fragrance, Glyceryl Stearate, Hamamelis Virginiana (Witch Hazel), Laureth-7, Magnesium Chloride, Mangifera Indica (Mango) Seed Butter, Mentha piperita (Peppermint) Leaf Oil, Olea Europaea (Olive) Fruit Oil, Olus Oil (vegetable), PEG-100 Stearate, Phenoxyethanol, Polyacrylamide, Stearic Acid.

QUESTIONS

info@ak47painrelief.com

WARNINGS

For external use only.

PACKAGE LABEL

AND PRODUCT BOX

BOX OF 10